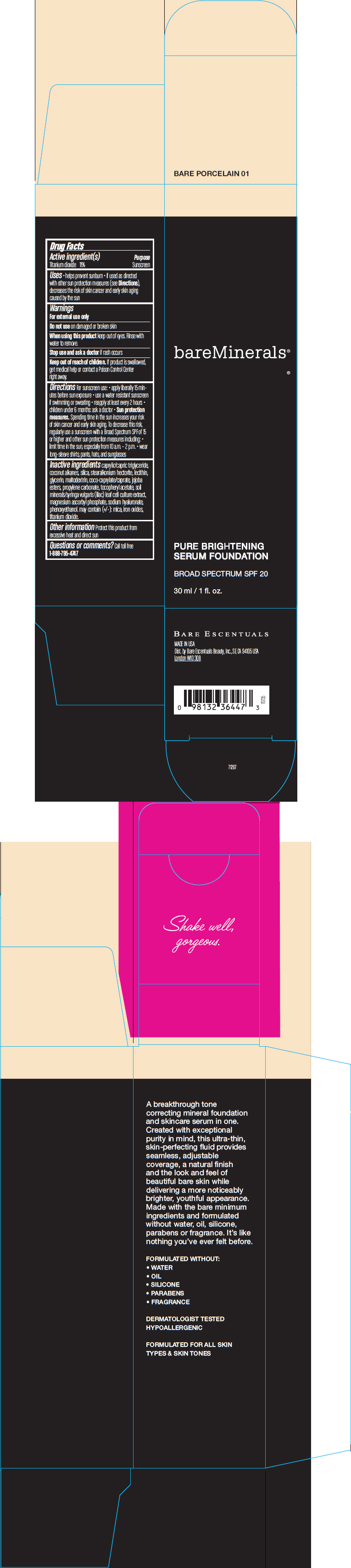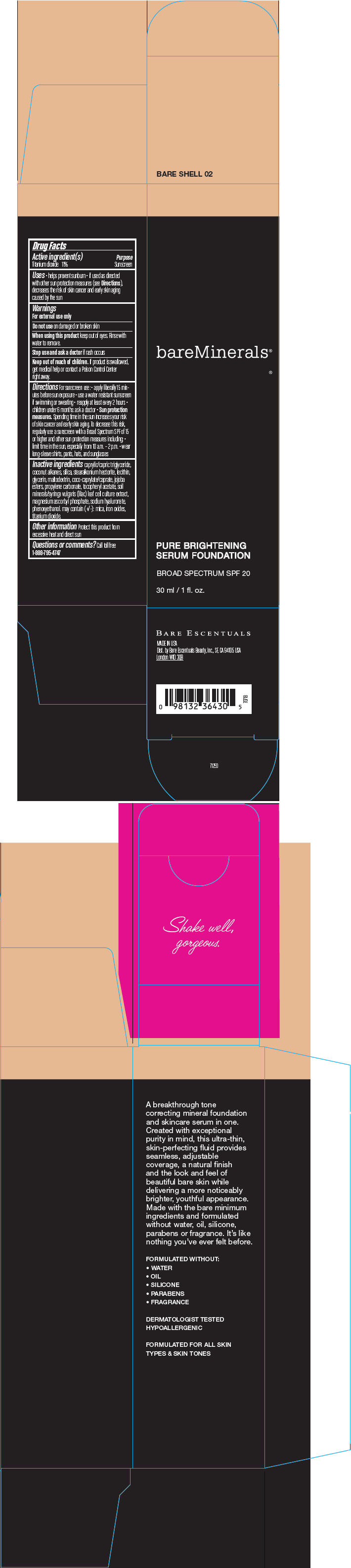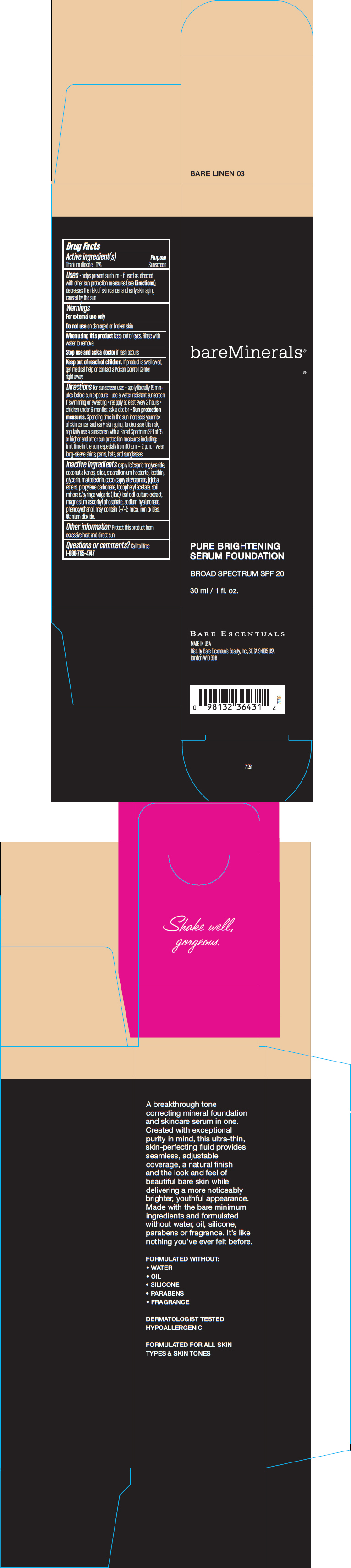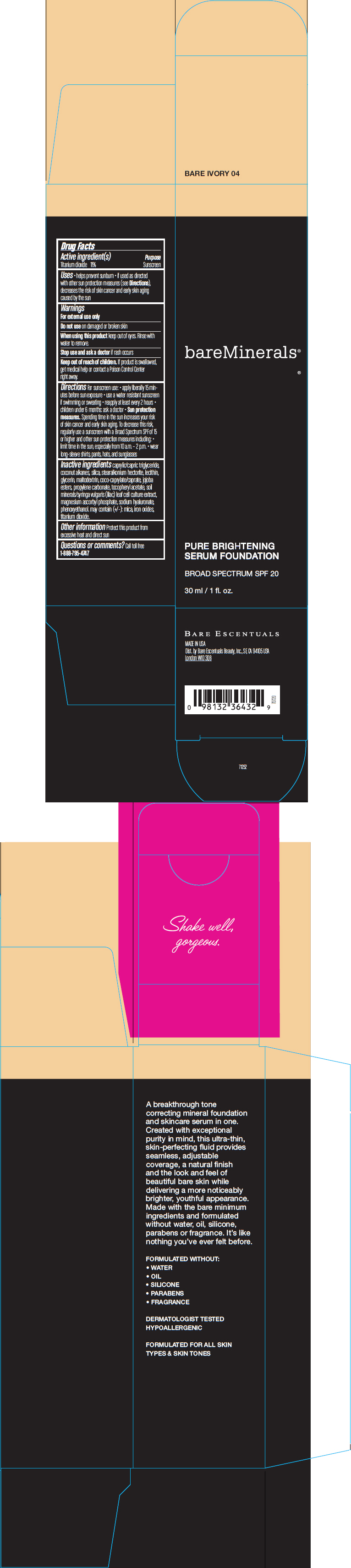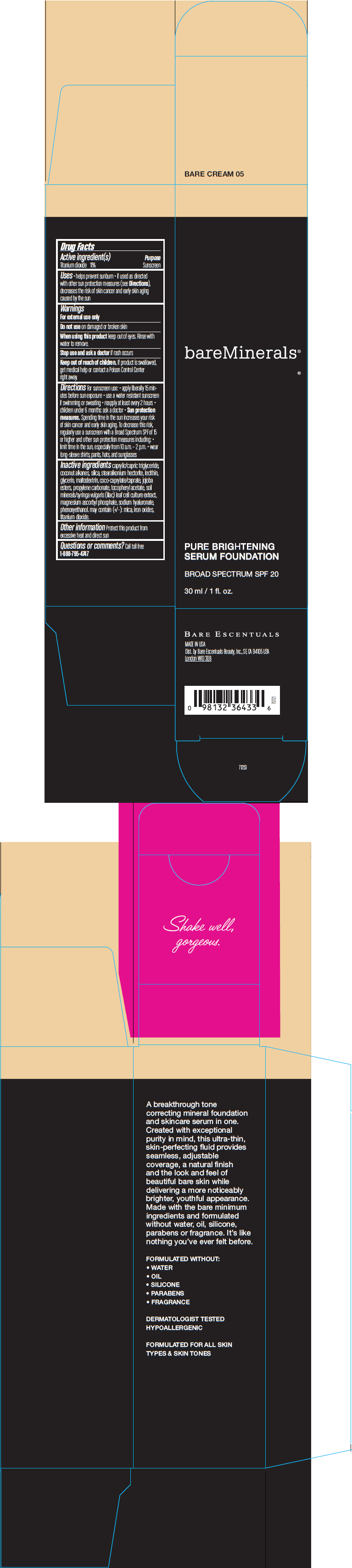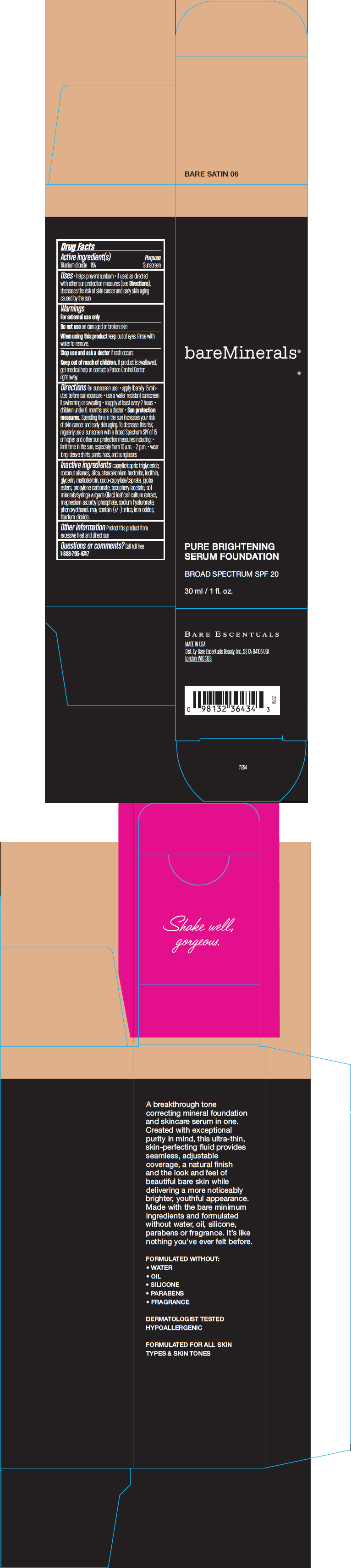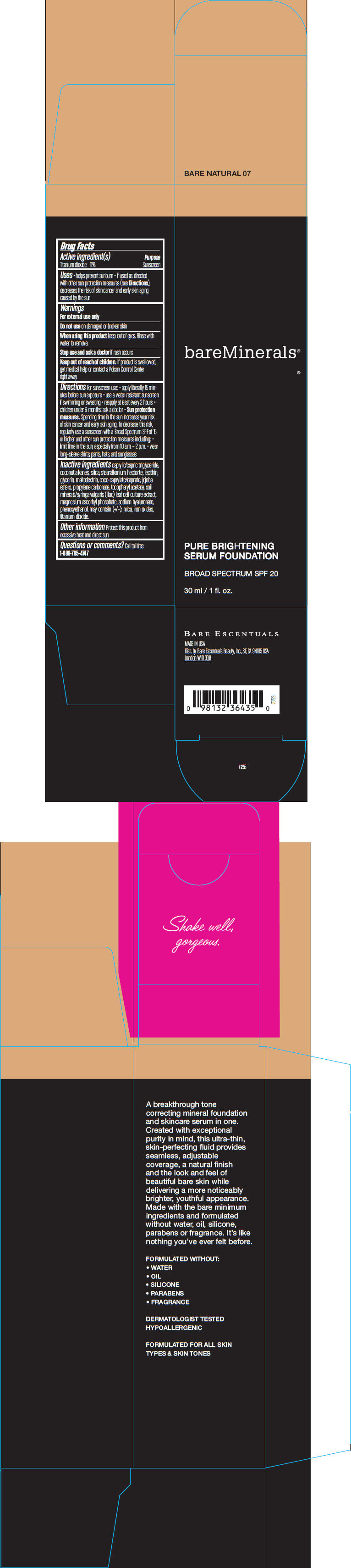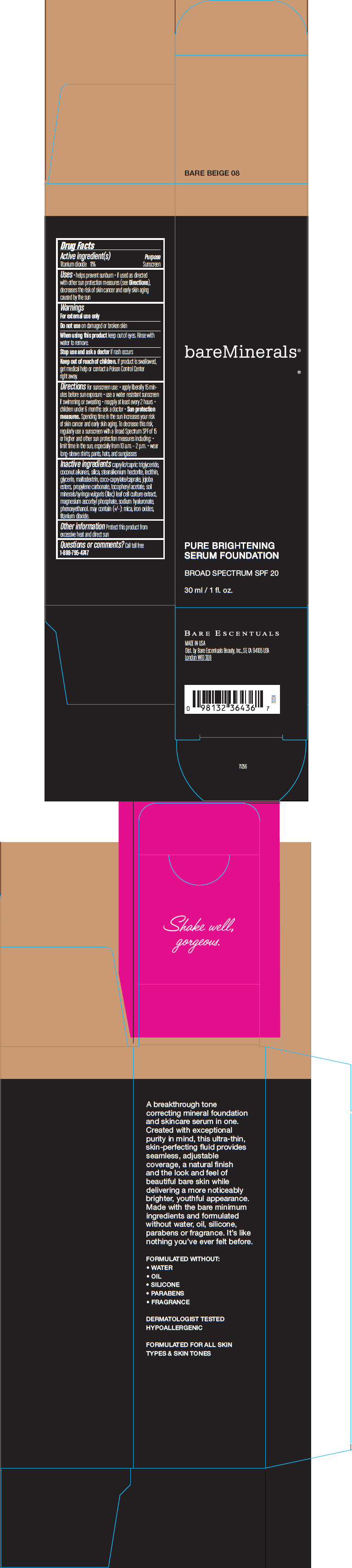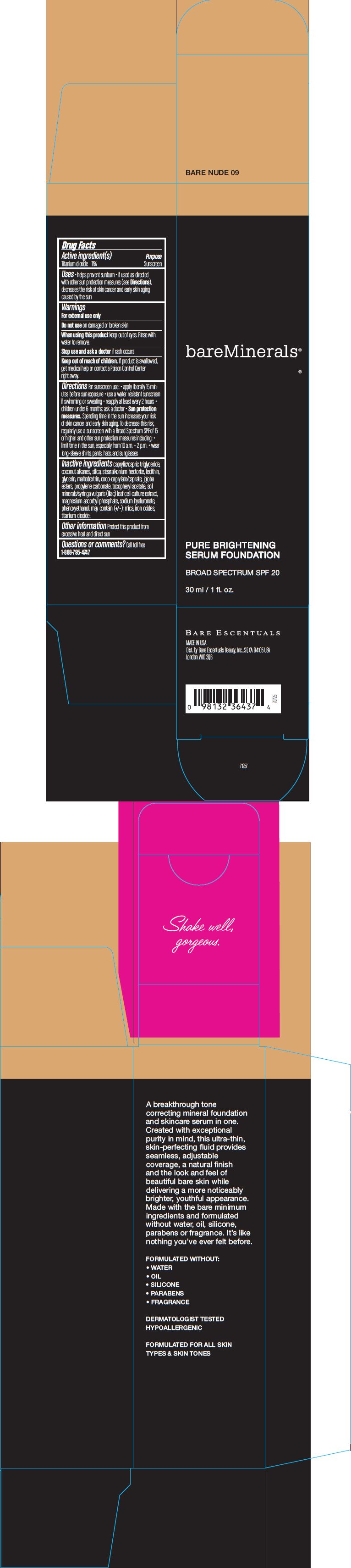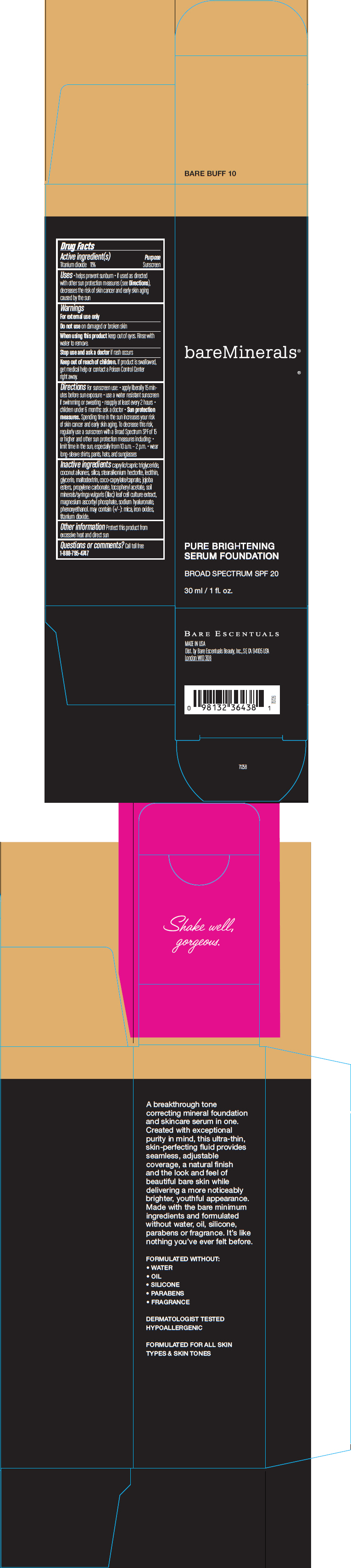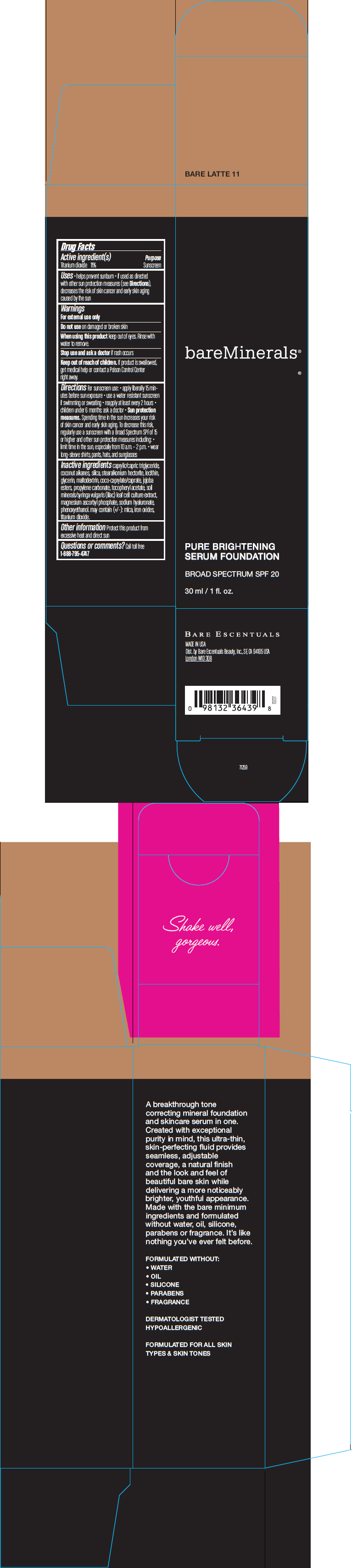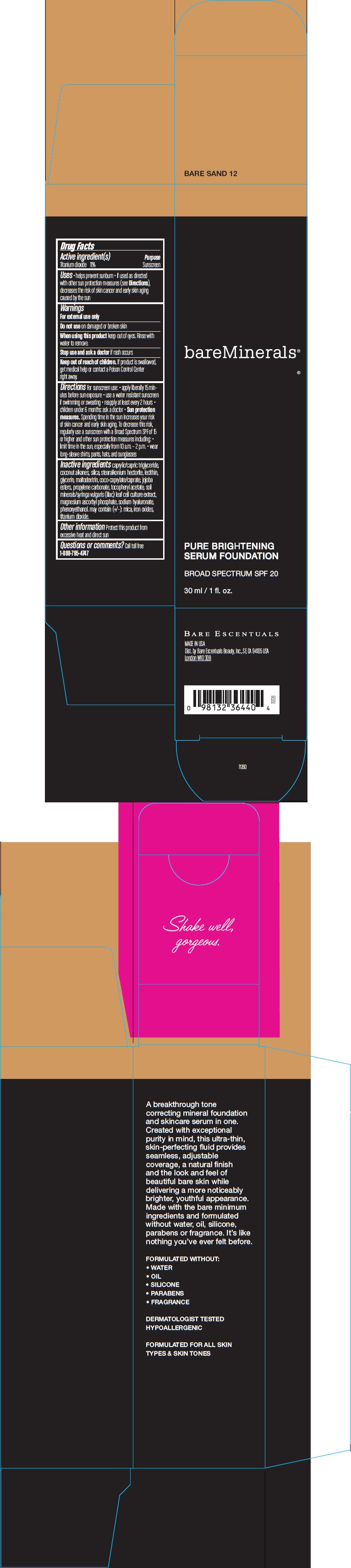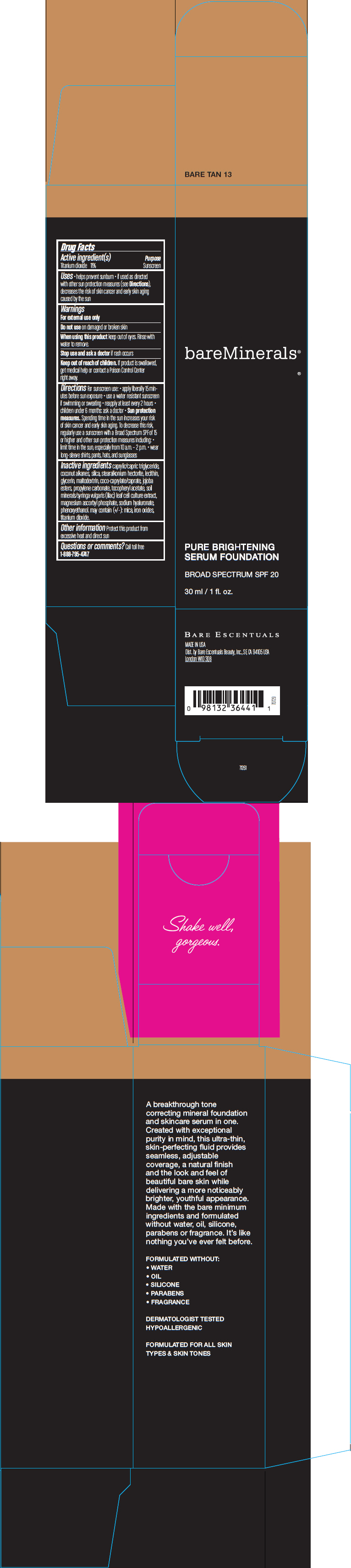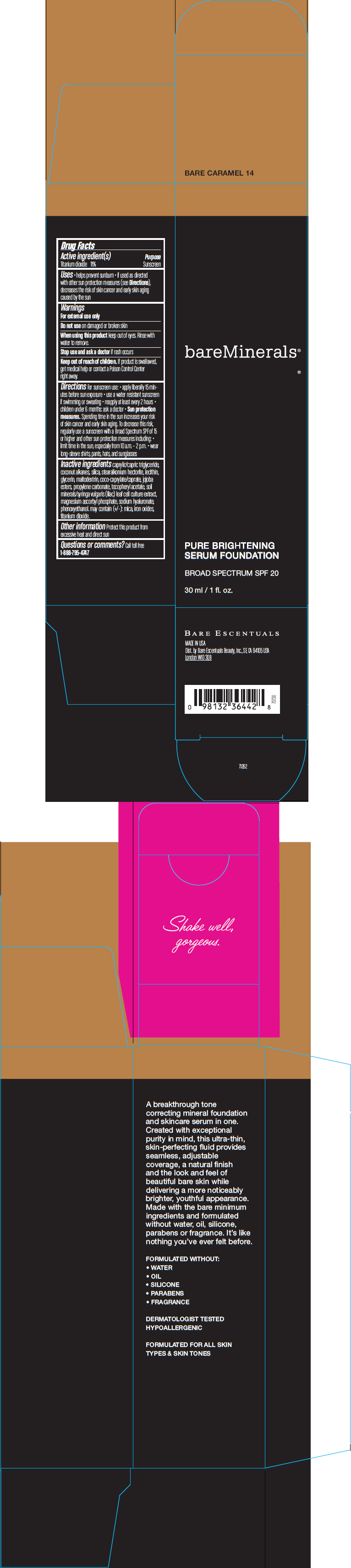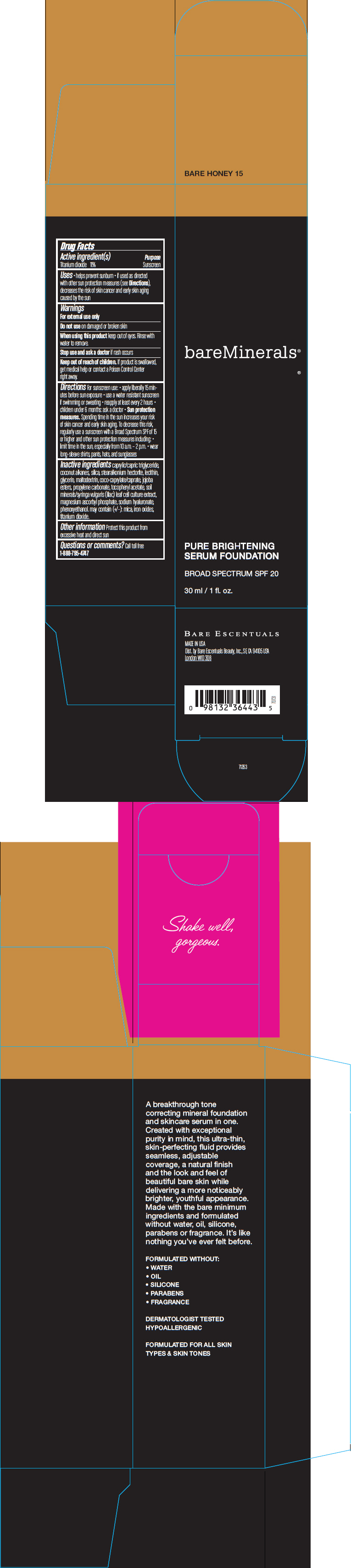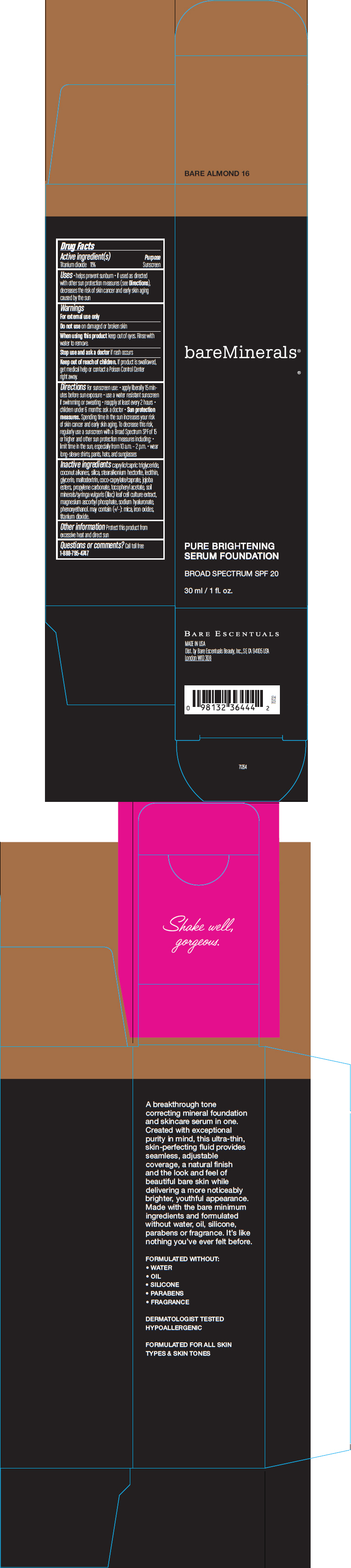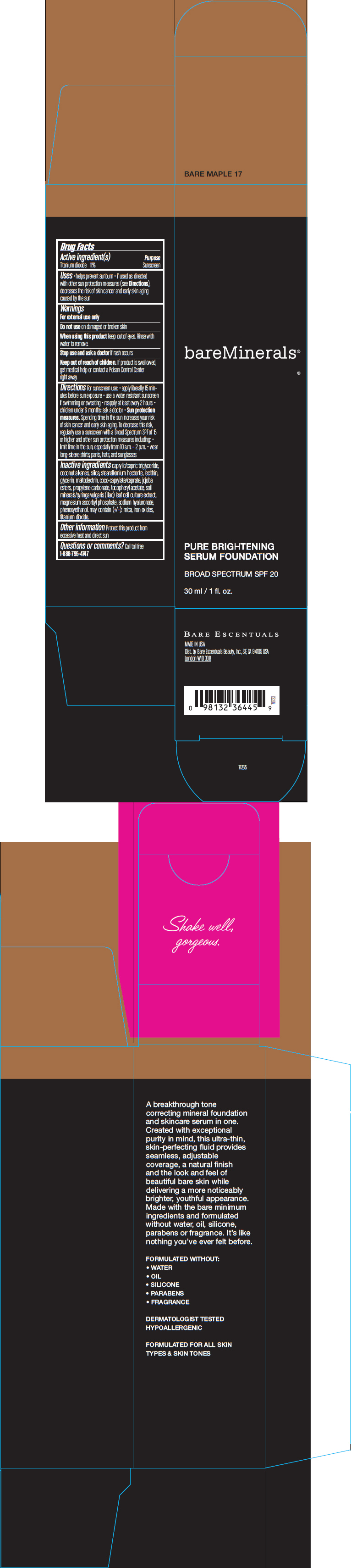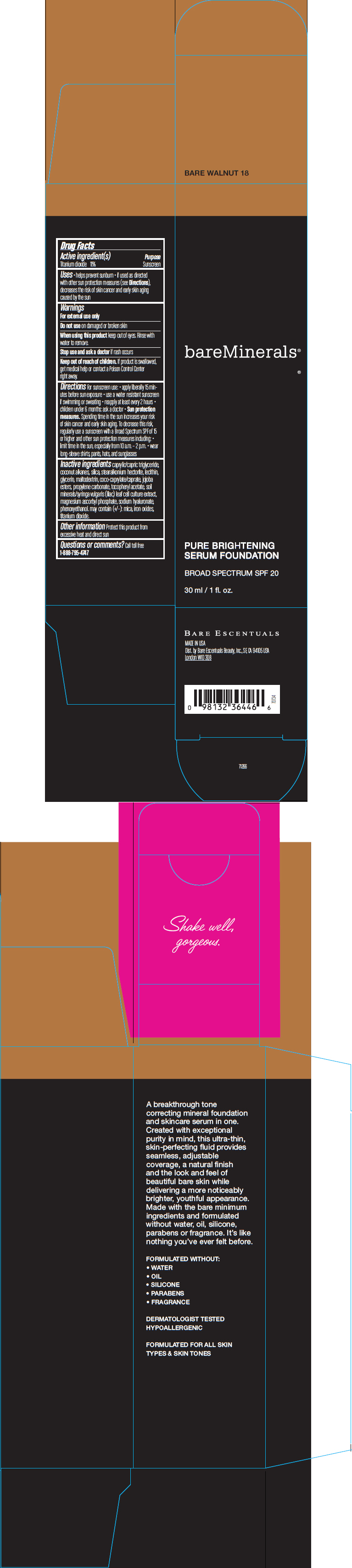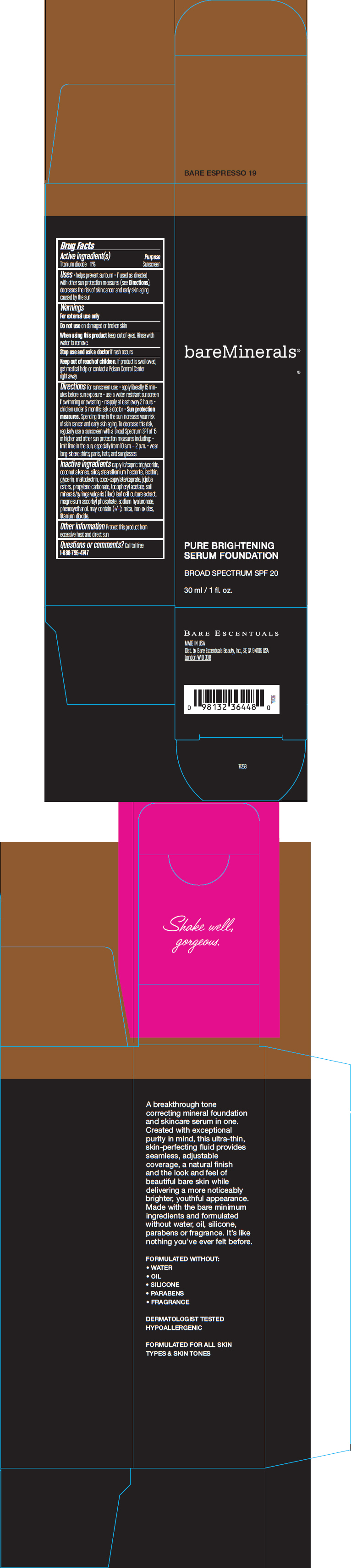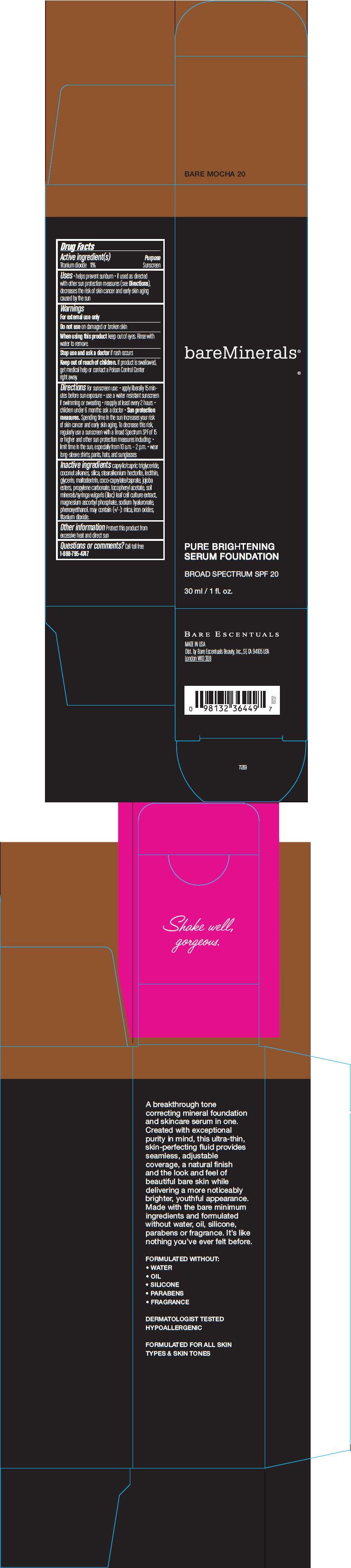 DRUG LABEL: bareMinerals bareSkin Pure Brightening Serum Foundation Broad Spectrum SPF 20 
NDC: 98132-730 | Form: LIQUID
Manufacturer: Bare Escentuals Beauty, Inc.
Category: otc | Type: HUMAN OTC DRUG LABEL
Date: 20140228

ACTIVE INGREDIENTS: Titanium Dioxide 110 mg/1 mL
INACTIVE INGREDIENTS: MEDIUM-CHAIN TRIGLYCERIDES; COCONUT ALKANES; SILICON DIOXIDE; STEARALKONIUM HECTORITE; GLYCERIN; MALTODEXTRIN; COCO-CAPRYLATE/CAPRATE; PROPYLENE CARBONATE; .ALPHA.-TOCOPHEROL ACETATE; MAGNESIUM ASCORBYL PHOSPHATE; HYALURONATE SODIUM; PHENOXYETHANOL; MICA; FERRIC OXIDE RED

bareMinerals® bareSkin Pure Brightening Serum Foundation Broad Spectrum SPF 20

Drug Facts

Active ingredient(s)

Titanium dioxide 11%

Purpose

Sunscreen

Uses

- helps prevent sunburn
- if used as directed with other sun protection measures (see Directions), decreases the risk of skin cancer and early skin aging caused by the sun

Warnings

For external use only

Do not use on damaged or broken skin

When using this product keep out of eyes. Rinse with water to remove.

Stop use and ask a doctor if rash occurs

Keep out of reach of children. If product is swallowed, get medical help or contact a Poison Control Center right away.

Directions

For sunscreen use:

- apply liberally 15 minutes before sun exposure
- use a water resistant sunscreen if swimming or sweating
- reapply at least every 2 hours
- children under 6 months: ask a doctor
- Sun protection measures. Spending time in the sun increases your risk of skin cancer and early skin aging. To decrease this risk, regularly use a sunscreen with a Broad Spectrum SPF of 15 or higher and other sun protection measures including:
  - limit time in the sun, especially from 10 a.m. – 2 p.m.
  - wear long-sleeve shirts, pants, hats, and sunglasses

Inactive ingredients

caprylic/capric triglyceride, coconut alkanes, silica, stearalkonium hectorite, lecithin, glycerin, maltodextrin, coco-caprylate/caprate, jojoba esters, propylene carbonate, tocopheryl acetate, soil minerals/syringa vulgaris (lilac) leaf cell culture extract, magnesium ascorbyl phosphate, sodium hyaluronate, phenoxyethanol. may contain (+/-): mica, iron oxides, titanium dioxide.

Other information

Protect this product from excessive heat and direct sun

Questions or comments?

Call toll free
1-888-795-4747

Dist. by Bare Escentuals Beauty, Inc., SF, CA 94105 USA

PRINCIPAL DISPLAY PANEL - 30 ml Bottle Carton - Bare Porcelain 01

bareMinerals®

PURE BRIGHTENING
SERUM FOUNDATION

BROAD SPECTRUM SPF 20

30 ml / 1 fl. oz.

PRINCIPAL DISPLAY PANEL - 30 ml Bottle Carton - Bare Shell 02

bareMinerals®

PURE BRIGHTENING
SERUM FOUNDATION

BROAD SPECTRUM SPF 20

30 ml / 1 fl. oz.

PRINCIPAL DISPLAY PANEL - 30 ml Bottle Carton - Bare Linen 03

bareMinerals®

PURE BRIGHTENING
SERUM FOUNDATION

BROAD SPECTRUM SPF 20

30 ml / 1 fl. oz.

PRINCIPAL DISPLAY PANEL - 30 ml Bottle Carton - Bare Ivory 04

bareMinerals®

PURE BRIGHTENING
SERUM FOUNDATION

BROAD SPECTRUM SPF 20

30 ml / 1 fl. oz.

PRINCIPAL DISPLAY PANEL - 30 ml Bottle Carton - Bare Cream 05

bareMinerals®

PURE BRIGHTENING
SERUM FOUNDATION

BROAD SPECTRUM SPF 20

30 ml / 1 fl. oz.

PRINCIPAL DISPLAY PANEL - 30 ml Bottle Carton - Bare Satin 06

bareMinerals®

PURE BRIGHTENING
SERUM FOUNDATION

BROAD SPECTRUM SPF 20

30 ml / 1 fl. oz.

PRINCIPAL DISPLAY PANEL - 30 ml Bottle Carton - Bare Natural 07

bareMinerals®

PURE BRIGHTENING
SERUM FOUNDATION

BROAD SPECTRUM SPF 20

30 ml / 1 fl. oz.

PRINCIPAL DISPLAY PANEL - 30 ml Bottle Carton - Bare Beige 08

bareMinerals®

PURE BRIGHTENING
SERUM FOUNDATION

BROAD SPECTRUM SPF 20

30 ml / 1 fl. oz.

PRINCIPAL DISPLAY PANEL - 30 ml Bottle Carton - Bare Nude 09

bareMinerals®

PURE BRIGHTENING
SERUM FOUNDATION

BROAD SPECTRUM SPF 20

30 ml / 1 fl. oz.

PRINCIPAL DISPLAY PANEL - 30 ml Bottle Carton - Bare Buff 10

bareMinerals®

PURE BRIGHTENING
SERUM FOUNDATION

BROAD SPECTRUM SPF 20

30 ml / 1 fl. oz.

PRINCIPAL DISPLAY PANEL - 30 ml Bottle Carton - Bare Latte 11

bareMinerals®

PURE BRIGHTENING
SERUM FOUNDATION

BROAD SPECTRUM SPF 20

30 ml / 1 fl. oz.

PRINCIPAL DISPLAY PANEL - 30 ml Bottle Carton - Bare Sand 12

bareMinerals®

PURE BRIGHTENING
SERUM FOUNDATION

BROAD SPECTRUM SPF 20

30 ml / 1 fl. oz.

PRINCIPAL DISPLAY PANEL - 30 ml Bottle Carton - Bare Tan 13

bareMinerals®

PURE BRIGHTENING
SERUM FOUNDATION

BROAD SPECTRUM SPF 20

30 ml / 1 fl. oz.

PRINCIPAL DISPLAY PANEL - 30 ml Bottle Carton - Bare Caramel 14

bareMinerals®

PURE BRIGHTENING
SERUM FOUNDATION

BROAD SPECTRUM SPF 20

30 ml / 1 fl. oz.

PRINCIPAL DISPLAY PANEL - 30 ml Bottle Carton - Bare Honey 15

bareMinerals®

PURE BRIGHTENING
SERUM FOUNDATION

BROAD SPECTRUM SPF 20

30 ml / 1 fl. oz.

PRINCIPAL DISPLAY PANEL - 30 ml Bottle Carton - Bare Almond 16

bareMinerals®

PURE BRIGHTENING
SERUM FOUNDATION

BROAD SPECTRUM SPF 20

30 ml / 1 fl. oz.

PRINCIPAL DISPLAY PANEL - 30 ml Bottle Carton - Bare Maple 17

bareMinerals®

PURE BRIGHTENING
SERUM FOUNDATION

BROAD SPECTRUM SPF 20

30 ml / 1 fl. oz.

PRINCIPAL DISPLAY PANEL - 30 ml Bottle Carton - Bare Walnut 18

bareMinerals®

PURE BRIGHTENING
SERUM FOUNDATION

BROAD SPECTRUM SPF 20

30 ml / 1 fl. oz.

PRINCIPAL DISPLAY PANEL - 30 ml Bottle Carton - Bare Espresso 19

bareMinerals®

PURE BRIGHTENING
SERUM FOUNDATION

BROAD SPECTRUM SPF 20

30 ml / 1 fl. oz.

PRINCIPAL DISPLAY PANEL - 30 ml Bottle Carton - Bare Mocha 20

bareMinerals®

PURE BRIGHTENING
SERUM FOUNDATION

BROAD SPECTRUM SPF 20

30 ml / 1 fl. oz.